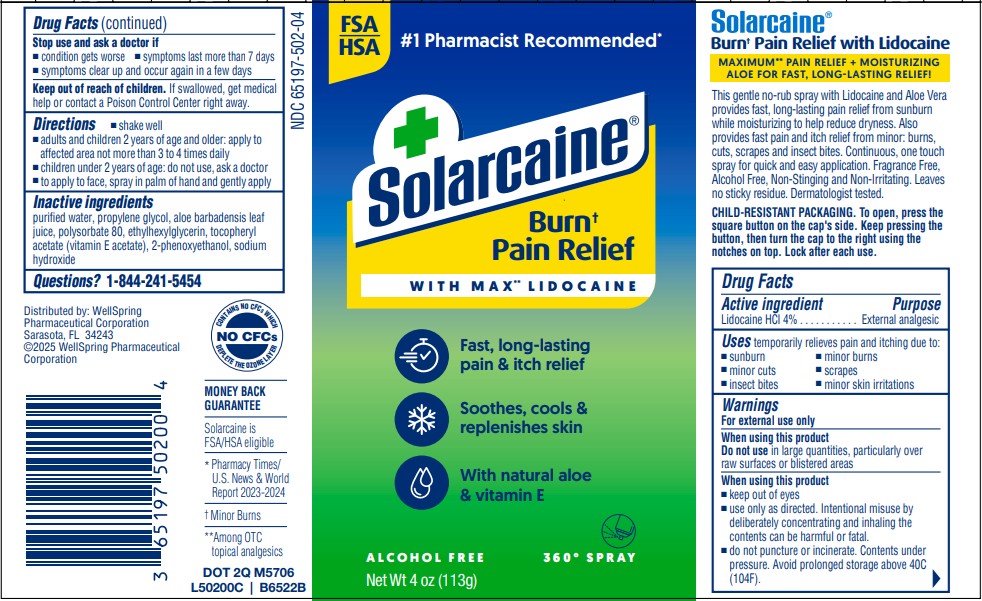 DRUG LABEL: Solarcaine Burn Pain Relief  4oz
NDC: 65197-502 | Form: SPRAY
Manufacturer: WellSpring Pharmaceutical Corporation
Category: otc | Type: HUMAN OTC DRUG LABEL
Date: 20251203

ACTIVE INGREDIENTS: LIDOCAINE HYDROCHLORIDE 4 g/100 g
INACTIVE INGREDIENTS: WATER; PROPYLENE GLYCOL; ALOE VERA LEAF; SODIUM HYDROXIDE; .ALPHA.-TOCOPHEROL ACETATE; POLYSORBATE 81; PHENOXYETHANOL; ETHYLHEXYLGLYCERIN

Solarcaine Burn Pain Relief Spray 4oz

Active Ingredients (w/w)

Lidocaine HCl 4%

Purpose

External Analgesic

Uses

temporarily relieves pain and itching due to:

- sunburn
- minor burns
- minor cuts
- scrapes
- insect bites
- minor skin irritations

Warnings

For external use only. When using this product

Do not use

in large quantities, particularly over raw surfaces or blistered areas

When using this product

- keep out of eyes
- use only as directed. Intentional misuse by deliberately concentrating and inhaling the contents can be harmful or fatal.
- do not puncture or incinerate. Contents under pressure. Avoid prolonged storage above 40°C (104°F).

Stop use and ask a doctor if

- condition gets worse
- symptoms last more than 7 days
- symptoms clear up and occur again in a few days

Keep out of reach of children

- If swallowed, get medical help or contact a Poison Control Center right away.

Directions

- shake well
- adults and children 2 years of age and older: apply to affected area not more than 3 to 4 times daily
- children under 2 years of age: do not use, ask a doctor
- to apply to face, spray in palm of hand and gently apply

Inactive ingredients

purified water, propylene glycol, aloe barbadensis leaf juice, polysorbate 80, ethylhexylglycerin, tocopheryl acetate (vitamin E acetate), 2-phenoxyethanol, sodium hydroxide

Questions?

1-844-241-5454

Distributed by:

WellSpring Pharmaceutical Corporation
Sarasota, FL 34243

© 2023 WellSpring Pharmaceutical Corporation
MONEY BACK GUARANTEE

Solarcaine is FSA/HSA eligible

PACKAGE LABEL. PRINCIPAL DISPLAY PANEL

#1 Pharmacist Recommended*

* Pharmacy Times/* U.S News & World

Report 2023-2024

DOT 2Q M5706

L50200C | B6522

CONTAINS NO CFCs WHICH
DEPLETE THE OZONE LAYER

Solarcaine Burn Pain Relief